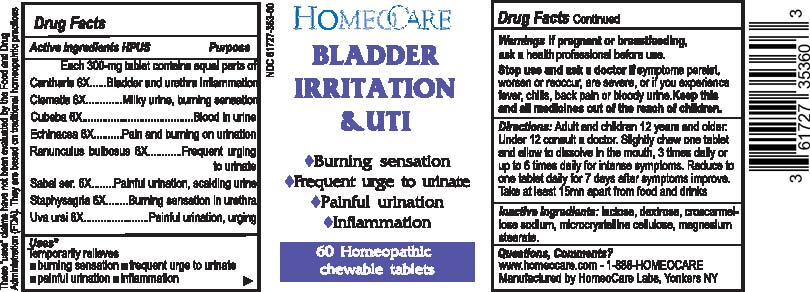 DRUG LABEL: Bladder Irritation and UTI
NDC: 61727-353 | Form: TABLET, CHEWABLE
Manufacturer: HomeoCare Laboratories, Inc.
Category: homeopathic | Type: HUMAN OTC DRUG LABEL
Date: 20190319

ACTIVE INGREDIENTS: SERENOA REPENS WHOLE 6 [hp_X]/60 1; PIPER CUBEBA FRUIT 6 [hp_X]/60 1; CLEMATIS RECTA FLOWERING TOP 6 [hp_X]/60 1; ARCTOSTAPHYLOS UVA-URSI LEAF 6 [hp_X]/60 1; DELPHINIUM STAPHISAGRIA SEED 6 [hp_X]/60 1; ECHINACEA ANGUSTIFOLIA 6 [hp_X]/60 1; LYTTA VESICATORIA 6 [hp_X]/60 1; RANUNCULUS BULBOSUS 6 [hp_X]/60 1
INACTIVE INGREDIENTS: MAGNESIUM STEARATE; CROSCARMELLOSE SODIUM; LACTOSE MONOHYDRATE; DEXTROSE; MICROCRYSTALLINE CELLULOSE

Bladder Irritation & UTI

Uses*

Temporarily relieves

- burning sensation
- frequent urge to urinate
- painful urination
- inflammation

Directions:

Adult and children 12 years and older:

Under 12 consult a doctor. Slightly chew one tablet and allow to dissolve in the mouth, 3 times daily or up to 6 times daily for intense symptoms. Reduce to one tablet daily for 7 days after symptoms improve. Take at least 15mn apart from food and drinks

Warnings

If pregnant or breastfeeding, ask a health professional before use.

Stop use and ask a doctor if symptoms persist, worsen or reoccur, are severe, or if you experience fever, chills, back pain or bloody urine. Keep this and all medicinces out of the reach of children.

Inactive ingredients:

lactose, dextrose, croscarmellose sodium, microcrystalline cellulose, magnesium stearate.

Questions, Comments?

www.homeocare.com - 1-888-HOMEOCARE

Manufactured by HomeoCare Labs, Yonkers NY

Drug Facts Active ingredients HPUS Purpose

Each 300-mg tablet contains equal parts of

Cantharis 6X......Bladder and urethra inflammation

Clematis 6X......Milky urine, burning sensation

Cubeba 6X......Blood in urine

Echinacea 6X......Pain and burning on urination

Ranunculus bulbosus 6X......Frequent urging to urinate

Sabal ser. 6X......Painful urination, scalding urine

Staphysagria 6X......Burning sensation in urethra

Uva ursi 6X......Painful urination, urging

Uses*

Temporarily relieves

- burning sensation
- frequent urge to urinate
- painful urination
- inflammation